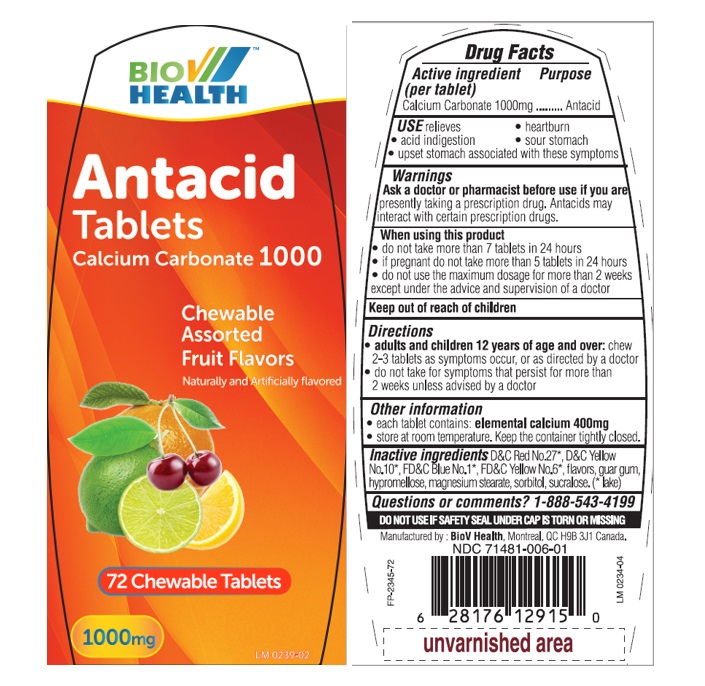 DRUG LABEL: Bio V Antacid Ultra Fruit 72ct
NDC: 71481-006 | Form: TABLET
Manufacturer: BioV Health Inc
Category: otc | Type: HUMAN OTC DRUG LABEL
Date: 20240404

ACTIVE INGREDIENTS: CALCIUM CARBONATE 1000 mg/1 1
INACTIVE INGREDIENTS: D&C RED NO. 27; D&C YELLOW NO. 10 ALUMINUM LAKE; FD&C BLUE NO. 1 ALUMINUM LAKE; FD&C YELLOW NO. 6; GUAR GUM; HYPROMELLOSE, UNSPECIFIED; MAGNESIUM STEARATE; SORBITOL; SUCRALOSE

Bio V Antacid Tablets ultra Fruit Flavors

Active ingredient (per tablet)

Calcium Carbonate 1000mg

Purpose

Antacid

USE

Relieves • acid indigestion • heartburn • sour stomach • upset stomach associated with these symptoms

Warnings

Ask a doctor or pharmacist before use if you arepresently taking a prescription drug. Antacids may interact with certain prescription drugs.

When using this product

- do not take more than 7 tablets in 24 hours.
- if pregnant do not take more than 5 tablets in 24 hours.
- do not use the maximum dosage for more than 2 weeks except under the advice and supervision of a doctor.

Keep out of of reach of children

Directions

- adults and children 12 years of age and over:chew 2-3 tablets as symtoms occur, or as directed by a doctor
- do not take for symtoms that persist for more than 2 weeks unless advised by a doctor

Other information

- each tablet contains: elemental calcium 400 mg.
- Store at room temperature. Keep the container tightly closed.

Inactive ingredients

D&C Red No.27*, D&C Yellow No.10*, FD&C Blue No.1*, FD&C Yellow No.6*, flavors, guar gum, hypromellose, magnesium stearate, sorbitol, sucralose. (*lake)

Questions or comments?

1-888-543-4199